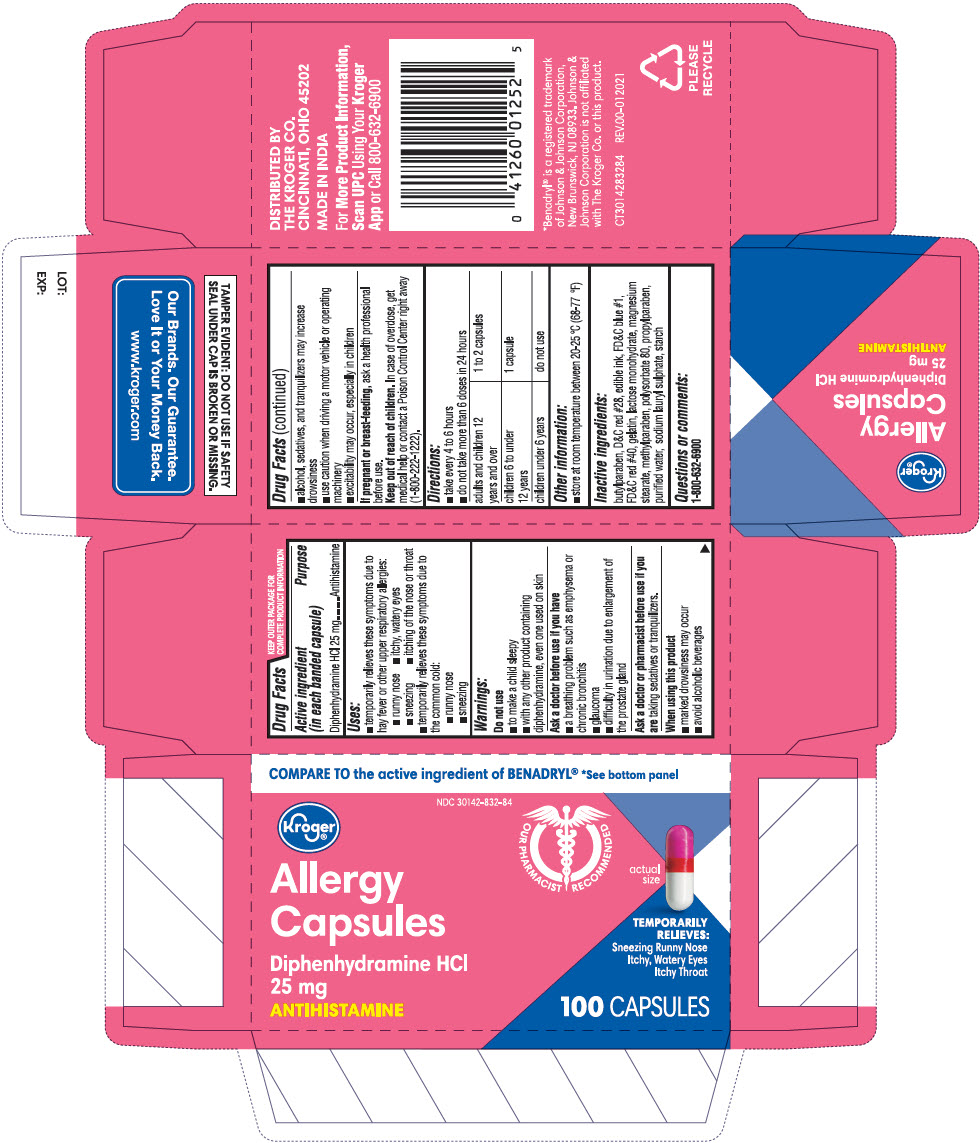 DRUG LABEL: Allergy Antihistamine
NDC: 30142-832 | Form: CAPSULE
Manufacturer: KROGER COMPANY
Category: otc | Type: HUMAN OTC DRUG LABEL
Date: 20240110

ACTIVE INGREDIENTS: DIPHENHYDRAMINE HYDROCHLORIDE 25 mg/1 1
INACTIVE INGREDIENTS: BUTYLPARABEN; D&C RED NO. 28; FD&C BLUE NO. 1; FD&C RED NO. 40; GELATIN, UNSPECIFIED; LACTOSE MONOHYDRATE; MAGNESIUM STEARATE; METHYLPARABEN; POLYSORBATE 80; PROPYLPARABEN; WATER; SODIUM LAURYL SULFATE

Allergy Antihistamine Capsules

Drug Facts

Active ingredient (in each banded capsule)

Diphenhydramine HCl 25 mg

Purpose

Antihistamine

Uses

- temporarily relieves these symptoms due to hay fever or other upper respiratory allergies:
  - runny nose
  - itchy, watery eyes
  - sneezing
  - itching of the nose or throat
- temporarily relieves these symptoms due to the common cold:
  - runny nose
  - sneezing

Warnings

Do not use

- to make a child sleepy
- with any other product containing diphenhydramine, even one used on skin

Ask a doctor before use if you have

- a breathing problem such as emphysema or chronic bronchitis
- glaucoma
- difficulty in urination due to enlargement of the prostate gland

Ask a doctor or pharmacist before use if you are taking sedatives or tranquilizers.

When using this product

- marked drowsiness may occur
- avoid alcoholic beverages
- alcohol, sedatives, and tranquilizers may increase drowsiness
- use caution when driving a motor vehicle or operating machinery
- excitability may occur, especially in children

PREGNANCY OR BREAST FEEDING

If pregnant or breast-feeding, ask a health professional before use.

Keep out of reach of children. In case of overdose, get medical help or contact a Poison Control Center right away.

Directions

- take every 4 to 6 hours
- do not take more than 6 doses in 24 hours

adults and children 12 years and over | 1 to 2 capsules
children 6 to under 12 years | 1 capsule
children under 6 years | do not use

Other information

- store at room temperature between 20-25 °C (68-77 °F)

Inactive ingredients

butylparaben, D&C Red #28, FD&C Blue #1, FD&C Red #40, gelatin, lactose monohydrate, magnesium stearate, methylparaben, polysorbate 80, propylparaben, purified water, sodium lauryl sulphate, starch

Questions or comments

1-800-632-6900

PRINCIPAL DISPLAY PANEL - 25 mg Capsule Bottle Carton

COMPARE TO the active ingredient of BENADRYL® *See bottom panel

NDC 30142-832-84

Kroger®

Allergy
Capsules

Diphenhydramine HCl
25 mg
ANTIHISTAMINE

OUR PHARMACIST RECOMMENDED

actual
size

TEMPORARILY
RELIEVES:
Sneezing Runny Nose
Itchy, Watery Eyes
Itchy Throat

100 CAPSULES